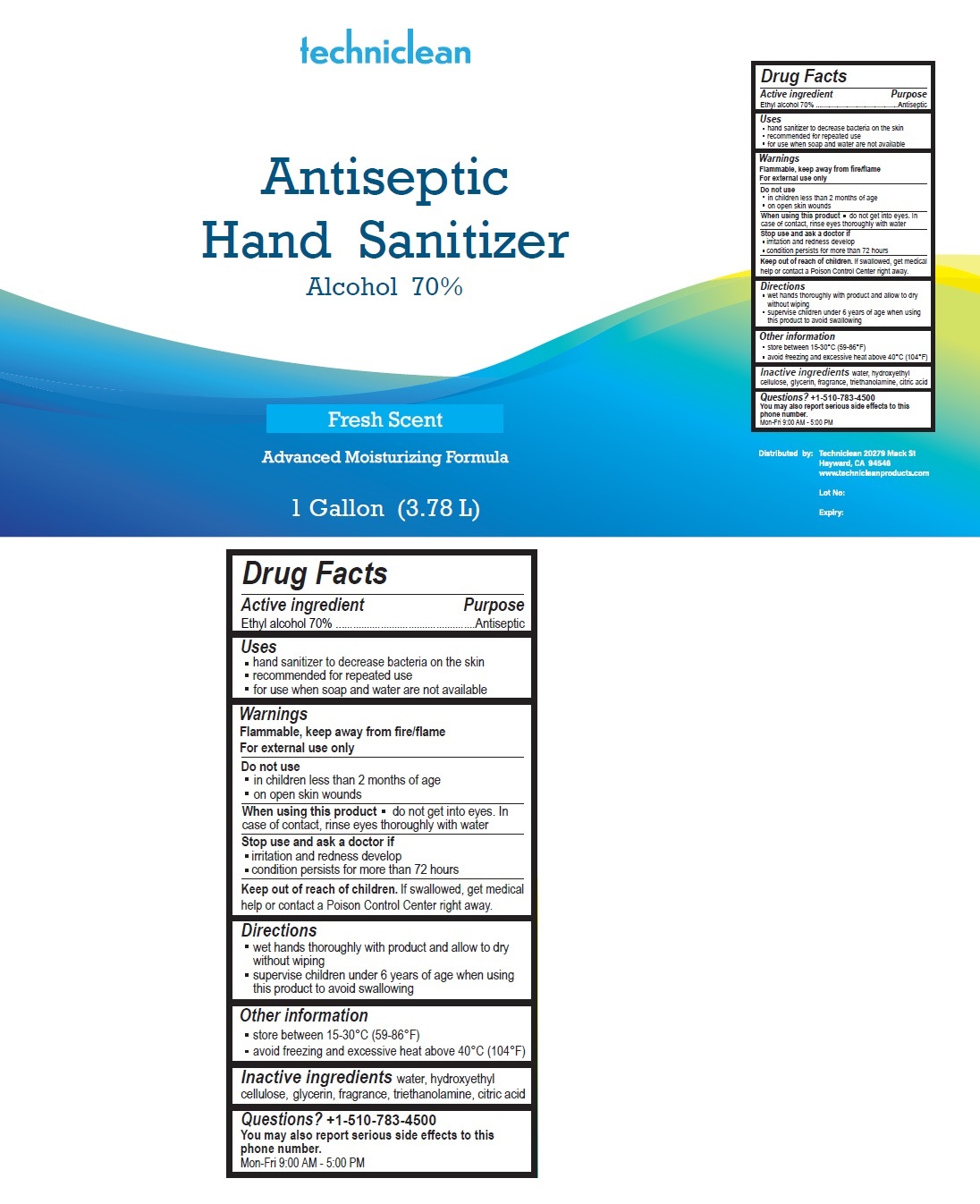 DRUG LABEL: TechniClean Antiseptic Hand Sanitizer
NDC: 77422-387 | Form: GEL
Manufacturer: Techniclean Products, Inc.
Category: otc | Type: HUMAN OTC DRUG LABEL
Date: 20200512

ACTIVE INGREDIENTS: ALCOHOL 0.7 L/1 L
INACTIVE INGREDIENTS: WATER; HYDROXYETHYL CELLULOSE, UNSPECIFIED; GLYCERIN; TROLAMINE; CITRIC ACID MONOHYDRATE

techniclean Antiseptic Hand Sanitizer

Active ingredient

Ethyl alcohol 70%

Purpose

Antiseptic

Uses

▪ hand sanitizer to decrease bacteria on the skin

▪ recommended for repeated use

▪ for use when soap and water are not available

Warnings

Flammable, keep away from fire/flame.

For external use only

Do not use

▪ in children less than 2 months of age

▪ on open skin wounds

When using this product ▪ do not get into eyes. In case of contact, rinse eyes thoroughly with water

Stop use and ask a doctor if

▪ irritation and redness develop

▪ condition persists for more than 72 hours.

Keep out of reach of children. If swallowed, get medical help or contact a Poison Control Center right away.

Directions

▪ wet hands thoroughly with product and allow to dry without wiping

▪ supervise children under 6 years of age when using this product to avoid swallowing

Other information

▪ store between 15-30°C (59-86°F)

▪ avoid freezing and excessive heat above 40°C (104°F)

INACTIVE INGREDIENT

Inactive ingredients water, hydroxyethyl cellulose, glycerin, fragrance, triethanolamine, citric acid

Questions? +1-510-783-4500

You may also report serious side effects to this phone number.

Mon-Fri 9.00AM - 5.00 PM

Fresh Scent

Advanced Moisturizing Formula

Distributed by: Techniclean 20279 Mack St

Hayward, CA 94546

www.technicleanproducts.com